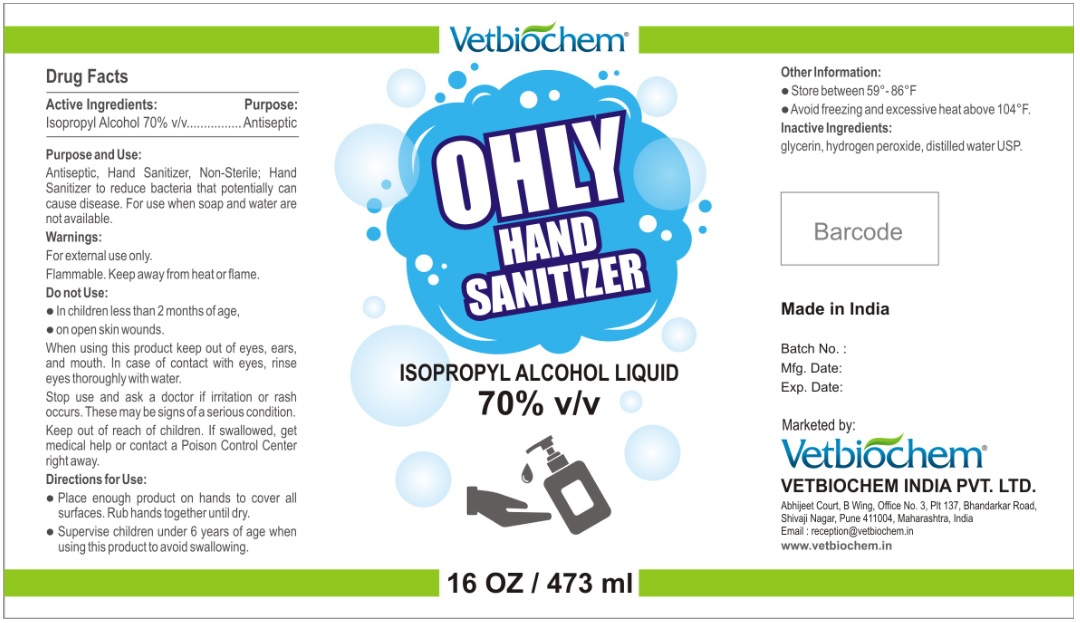 DRUG LABEL: OHLY HAND SANITIZER
NDC: 90111-001 | Form: LIQUID
Manufacturer: Vetbiochem India Private Limited
Category: otc | Type: HUMAN OTC DRUG LABEL
Date: 20200819

ACTIVE INGREDIENTS: ISOPROPYL ALCOHOL 70 mL/100 mL
INACTIVE INGREDIENTS: GLYCERIN; HYDROGEN PEROXIDE; WATER

OHLY HAND SANITIZER

Active Ingredients:

Isopropyl Alcohol 70% v/v

Purpose:

Antiseptic

Purpose and Use:

Antiseptic, Hand Sanitizer, Non-Sterile; Hand Sanitizer to reduce bacteria that potentially can cause disease. For use when soap and water are not available.

Warnings:

For external use only.

Flammable. Keep away from heat or flame.

Do not Use:

• In children less than 2 months of age,

• on open skin wounds.

When using this product keep out of eyes, ears, and mouth. In case of contact with eyes, rinse eyes thoroughly with water.

Stop use and ask a doctor if irritation or rash occurs. These may be signs of a serious condition.

Keep out of reach of children. If swallowed, get medical help or contact a Poison Control Center right away.

Directions for Use:

- Place enough product on hands to cover all surfaces. Rub hands together until dry.
- Supervise children under 6 years of age when using this product to avoid swallowing.

Other Information:

- Store between 59°-86°F
- Avoid freezing and excessive heat above 104°F.

Inactive Ingredients:

glycerin, hydrogen peroxide, distilled water USP.

Made in India

Marketed by:

Vetbiochem®

VETBIOCHEM INDIA PVT. LTD.

Abhijeet Court, B Wing, Office No. 3, Plt 137, Bhandarkar Road,

Shivaji Nagar, Pune 411004, Maharashtra, India

Email : reception@vetbiochem.in

www.vetbiochem.in